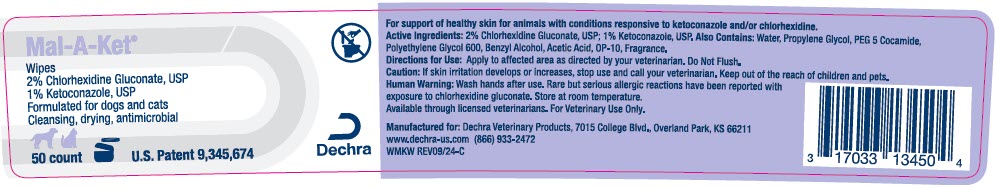 DRUG LABEL: Mal-A-Ket Wipes
NDC: 17033-134 | Form: CLOTH
Manufacturer: Dechra Veterinary Products
Category: animal | Type: OTC ANIMAL DRUG LABEL
Date: 20230504

ACTIVE INGREDIENTS: CHLORHEXIDINE GLUCONATE 20 mg/1 1; KETOCONAZOLE 10 mg/1 1

Mal-A-Ket® Wipes

VETERINARY INDICATIONS

For support of healthy skin for animals with conditions responsive to ketoconazole and/or chlorhexidine.

Active Ingredients: 2% Chlorhexidine Gluconate, USP; 1% Ketoconazole, USP.

INACTIVE INGREDIENT

Also Contains: Purified Water, Propylene Glycol, PEG 5 Cocamide, Polyethylene Glycol 600, Benzyl Alcohol, Acetic Acid, OP-10, Fragrance.

DOSAGE AND ADMINISTRATION

Directions for Use: Apply to affected area as directed by your veterinarian.

SAFE HANDLING WARNING

Caution: If skin irritation develops or increases, stop use and call your veterinarian. Keep out of the reach of children and pets.

WARNINGS

Human Warning: Wash hands after use. Rare but serious allergic reactions have been reported with exposure to chlorhexidine gluconate. Store at room temperature.

Available through licensed veterinarians. For Veterinary Use Only.

Manufactured for: Dechra Veterinary Products, 7015 College Blvd., Overland Park, KS 66211
www.dechra-us.com (866) 933-2472

WMKW REV09/24-C

PRINCIPAL DISPLAY PANEL - 50 Wipe Jar Label

Mal-A-Ket®

Wipes
2% Chlorhexidine Gluconate, USP
1% Ketoconazole, USP
Formulated for dogs and cats
Cleansing, drying, antimicrobial

50 count

U.S. Patent 9,345,674

Dechra